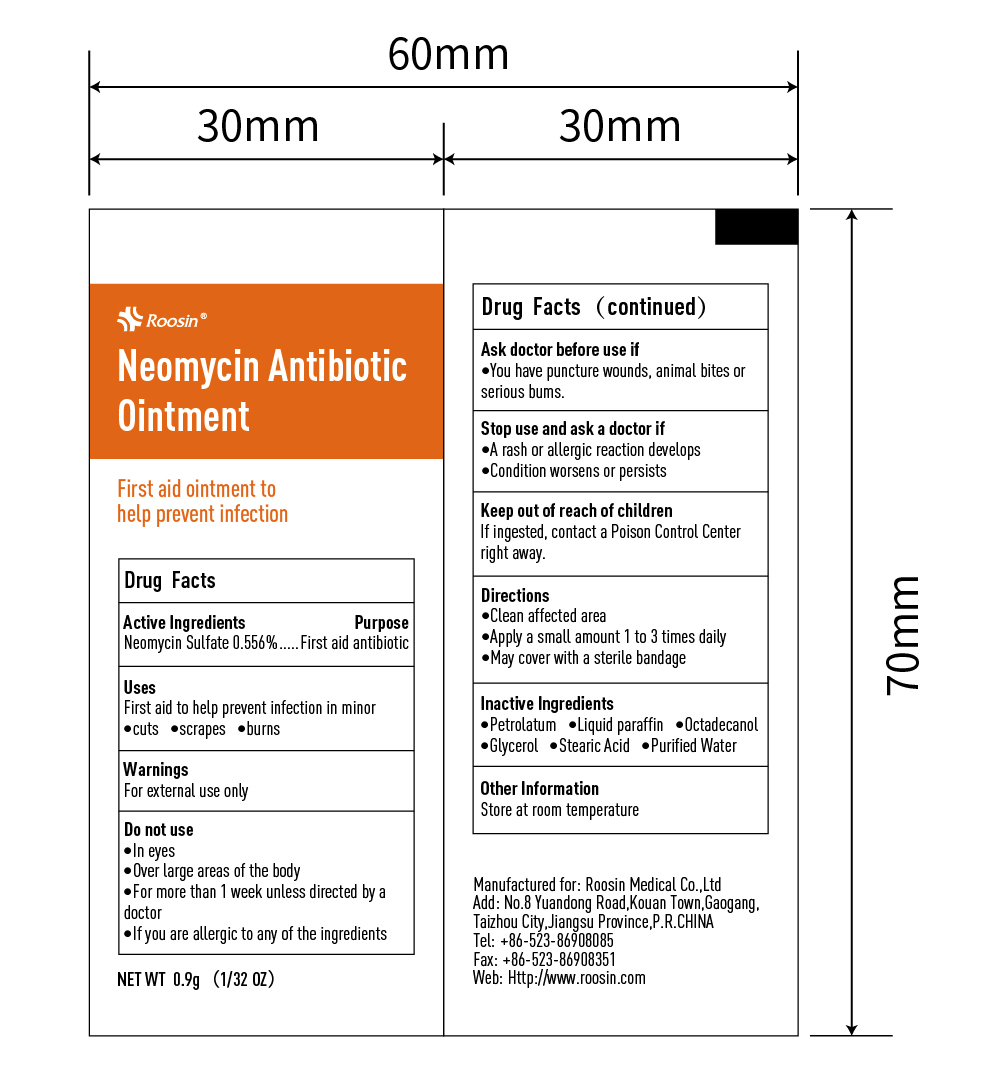 DRUG LABEL: Roosin Neomycin Antibiotic
NDC: 81552-001 | Form: OINTMENT
Manufacturer: ROOSIN MEDICAL CO., LTD
Category: otc | Type: HUMAN OTC DRUG LABEL
Date: 20211215

ACTIVE INGREDIENTS: NEOMYCIN SULFATE 0.556 g/100 g
INACTIVE INGREDIENTS: PETROLATUM; PARAFFIN; OCTADECANOL (MIXTURE OF ISOMERS); WATER; STEARIC ACID; GLYCEROL FORMAL

81552-001 Neomycin

Active Ingredient

Neomycin Sulfate 0.556%

Purpose

First Aid Antibiotic

Use

First aid to help prevent infection in minor cuts scrapes burns

WARNINGS

For external use only

Do not use

- In eyes
- Over large areas of the body
- For more than one week unless directed by a doctor
- If you are allergic to any of the ingredients

Ask doctor before use if you have puncture wounds, animal bites, or serious burns

Stop use an ask a doctor if

- A rash or allergic reaction develops
- Condition worsens or persists

Keep out of reach of children. If ingested, get medical help or contact a poison control center right away

Directions

Clean affected area

Apply a small amount 1-3 times daily

May cover with a sterile bandage

Other information

Store at room temperatuure

Inactive ingredients

Petrolactum, Liquid Paraffin, Octadecanol, Glycerol, Stearic Acid, Purified Water